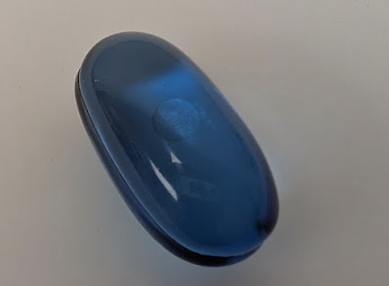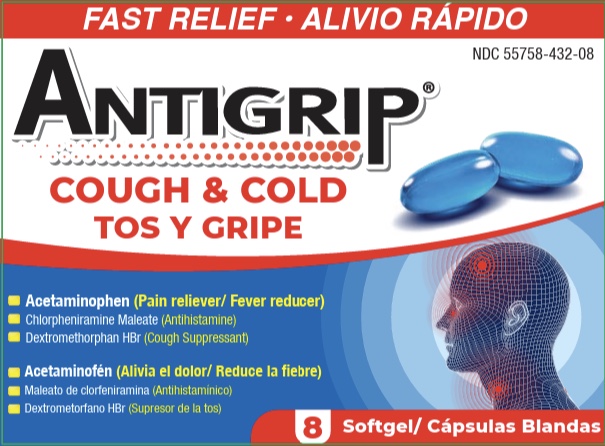 DRUG LABEL: Antigrip
NDC: 55758-432 | Form: CAPSULE, GELATIN COATED
Manufacturer: Pharmadel LLC
Category: otc | Type: HUMAN OTC DRUG LABEL
Date: 20250801

ACTIVE INGREDIENTS: CHLORPHENIRAMINE MALEATE 2 mg/1 1; DEXTROMETHORPHAN HYDROBROMIDE 10 mg/1 1; ACETAMINOPHEN 325 mg/1 1
INACTIVE INGREDIENTS: SORBITAN; TITANIUM DIOXIDE; FD&C BLUE NO. 1; GELATIN; GLYCERIN; POLYETHYLENE GLYCOL, UNSPECIFIED; POVIDONE; PROPYLENE GLYCOL; SORBITOL; WATER; D&C RED NO. 33

Antigrip Cold & Cough Gelcaps (Apta)

Active ingredients & Purposes

.

PURPOSE

Active ingredients (in each gel Softgel) | Purposes
Acetaminophen 325 mg ............ | Pain reliever/ fever reducer
Chlorpheniramine maleate 2 mg .......... | Antihistamine
Dextromethorphan HBr 10 mg.......... | Cough suppressant

Uses

Temporarily relieves common cough and cold symptoms due to

- minor aches and pain
- headache
- runny nose
- sneezing
- minor throat and bronchial irritation
- temporarily reduces fever

Warnings

Liver warning: This product contains acetaminophen. Severe liver damage may occur if

- adult takes more than 4 doses in 24 hours, which is the maximum daily amount for this product
- child takes more than 5 doses in 24 hours
- taken with other drugs containing acetaminophen
- adult has 3 or more alcoholic drinks everyday while using this product Allergy alert: Acetaminophen may cause severe skin reactions. Symptoms may include:
- skin reddening
- blisters
- rash If a skin reaction occurs, stop use and seek medical help right away.

Do not use

- with any other drug containing acetaminophen (prescription or nonprescription). If you are not sure whether a drug contains acetaminophen, ask a doctor or pharmacist.
- if you are now taking prescription monoamine oxidase inhibitors (MAOI) (certain drugs for depression, psychiatric, or emotional conditions or Parkinson’s disease), or for 2 weeks after stopping the MAOI drug. If you do not know if your prescription drug contains an MAOI, ask your doctor or pharmacist before taking this product.

Ask a doctor before use if the user

- is a child with pain from arthritis
- has liver disease
- has glaucoma
- has a breathing problem such as emphysema or chronic bronchitis
- has difficulty in urination due to enlargement of the prostate gland
- has a persistent or chronic cough such as occurs with smoking, asthma, or emphysema
- has a cough that is accompanied by excessive phlegm (mucus)
- is taking sedatives or tranquilizers

Ask a doctor or pharmacist before use if the user

is taking the blood thinning drug warfarin

When using this product

- may cause marked drowsiness
- may cause excitability, especially in children
- may cause drowsiness; alcohol, sedatives, and tranquilizers may increase the drowsiness effect
- avoid alcoholic beverages while taking this product
- use caution when driving a motor vehicle or operating machinery

Stop use and ask a doctor If

- pain or cough gets worse or lasts more than 5 days (children) or 7 days (adults)
- fever gets worse or lasts more than 3 days
- redness or swelling is present
- new symptoms occur
- a cough comes back or occurs with a rash headache that lasts. These could be signs of a serious condition.

If pregnant orbreast-feeding,

ask a health professional before use.

KEEP OUT OF REACH OF CHILDREN.

In case of an accidental overdose, get medical help or contact a Poison Control Center right away. Prompt medical attention is critical for adults as well as for children even if you do not notice any signs or symptoms.

Directions

- take each dose with plenty of water

Age | Dose
Adults and children 12 years and older | 2 softgels, every 6 hours not to exceed 4 doses in 24 hours
children 6 to under 12 years of age | 1 softgel, every 4 hours not to exceed 5 doses in 24 hours
children under 6 years of age | do not use

Other Information

- store between 68-77°F (20-25"C)
- avoid excessive heat

Inactive Ingredients

D&C red #33, FD&C blue #1, gelatin, glycerin, polyethylene glycol, povidone, propylene glycol, sorbitol sorbitan solution, titanium dioxide, water

Dist by/ por:

PHARMADEL LLC

New Castle, DE 19720

Questions/ Preguntas? +1-866-359-3478